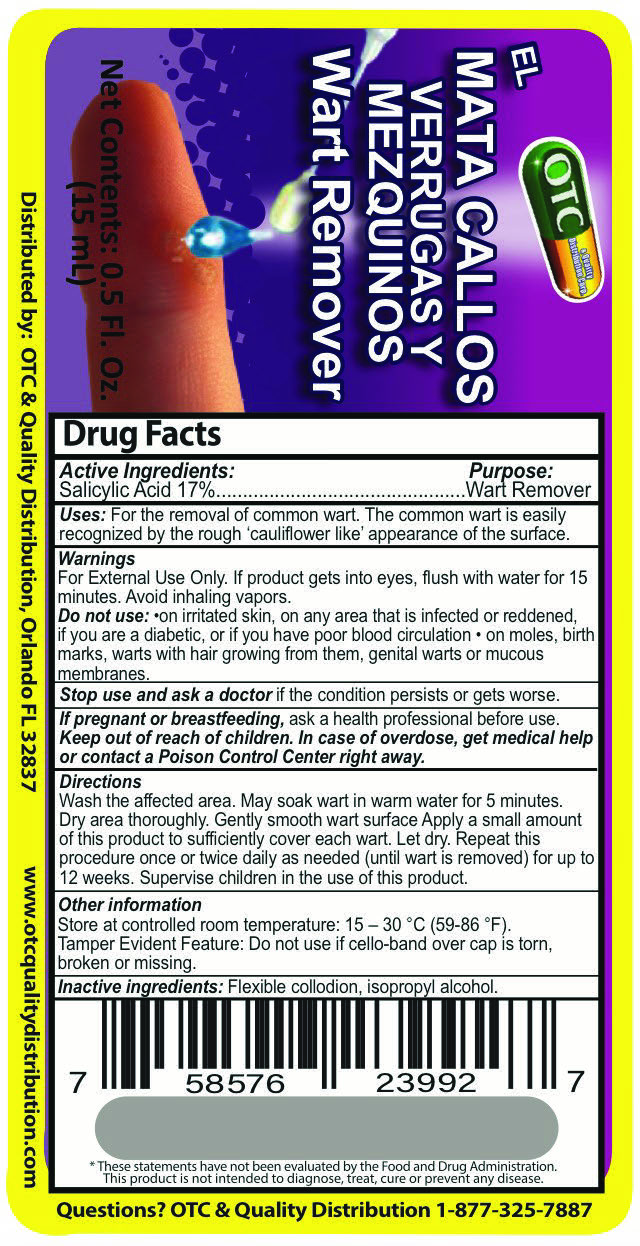 DRUG LABEL: El Mata Callos
NDC: 69469-017 | Form: SOLUTION
Manufacturer: Vitamex USA, Corp
Category: otc | Type: HUMAN OTC DRUG LABEL
Date: 20250623

ACTIVE INGREDIENTS: SALICYLIC ACID 170 mg/1 mL
INACTIVE INGREDIENTS: CASTOR OIL; CAMPHOR (SYNTHETIC); ISOPROPYL ALCOHOL; ALCOHOL

El Mata Callos 0.5oz

Drug Facts

Active Ingredients: Purpose:

Salicylic Acid 17% Wart Remover

Uses

Uses: For the removal of common wart. The common wart is easily recognized by the rough "cauliflower like" appearance of the surface.

Warnings

For External Use Only. If product gets into eyes, flush with water for 15 minutes. Avoid inhailing vapors.

Do not use: on irritated skin, on any area that is infected or reddened, if you are a diabeticm or if you have poor blood circulation, on moles, birth marks, warts with hair growing from them, genital warts or muccous membranes.

If pregnant or breastfeeding, ask a health professional before use.

Keep out of reach of children. In case of overdose, get medical help or contact a Poison control center right away.

Directions

Wash the affected area. May soak wart in warm water for 5 minutes. Dry area throughly. Gently smooth wart surface. Apply a small amount of this product to sufficiently cover each wart. Let dry. Repeat this procedure once or twice dialy as needed (until wart is removed) for up to 12 weeks. Supervise children in the use of this product,

Directions

Wash the affected area. May soak wart in warm water for 5 minutes. Dry area throughly. Gently smooth wart surface. Apply a small amount of this product to sufficiently cover each wart. Let dry. Repeat this procedure once or twice dialy as needed (until wart is removed) for up to 12 weeks. Supervise children in the use of this product,

Other information

Store at controlled room temperature: 15-30°C (59-86°F).

Tamper Evident Feature

Inactive Ingredients

Inactive Ingredients: Flexible Collodion, Isopropyl Alcohol

Dosage

Directions:

Wash the affected area. May soak wart in warm water for 5 minutes. Dry area throughly. Gently smooth wart surface. Apply a small amount of this product to sufficiently cover each wart. Let dry. Repeat this procedure once or twice dialy as needed (until wart is removed) for up to 12 weeks. Supervise children in the use of this product,

El Mata Callos Verrugas Y Mezquinos

Wart Remover

Net Contents: 0.5 Fl. Oz. (15mL)